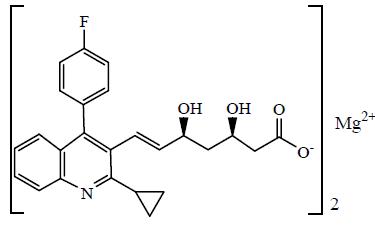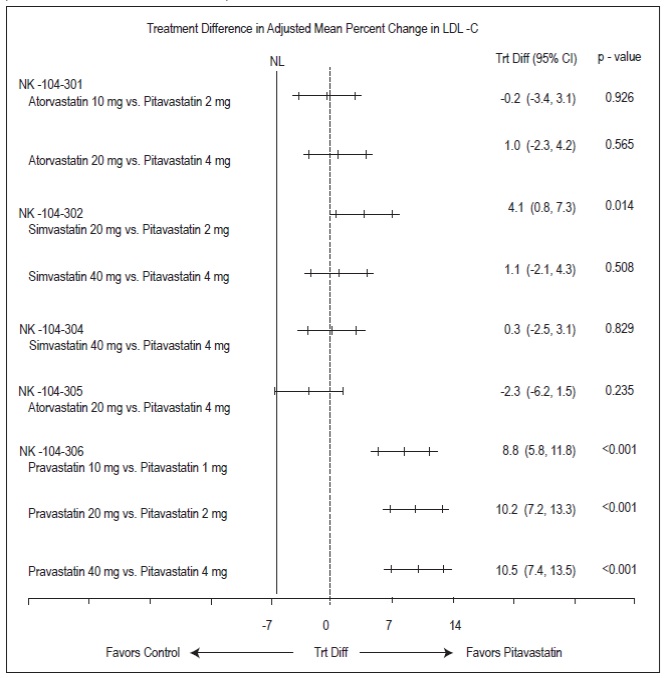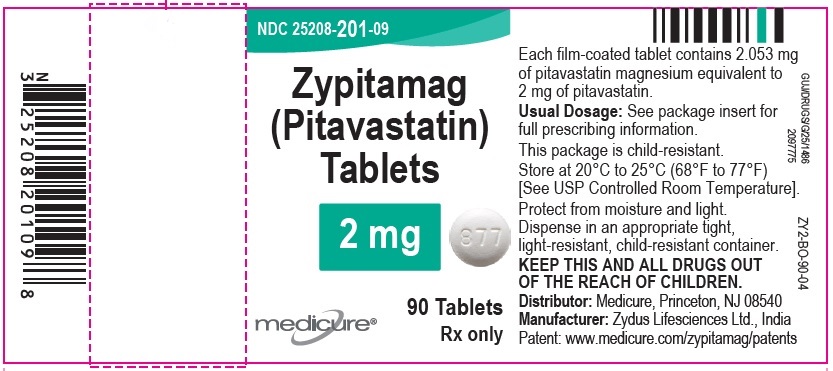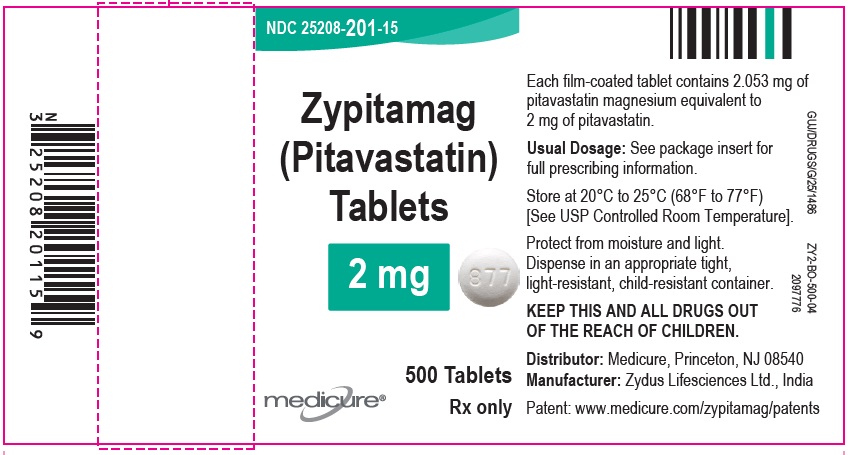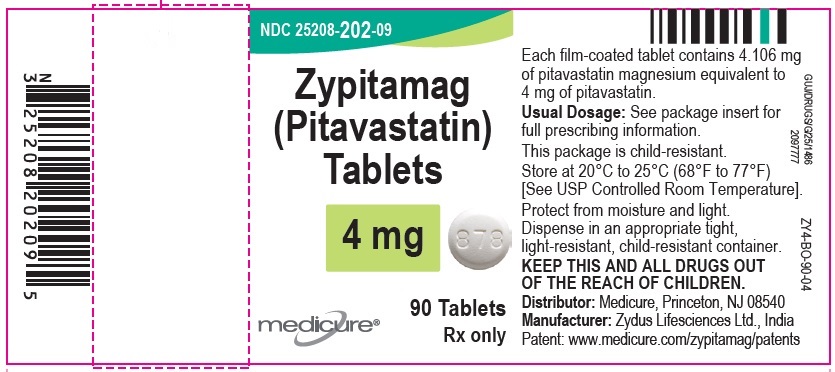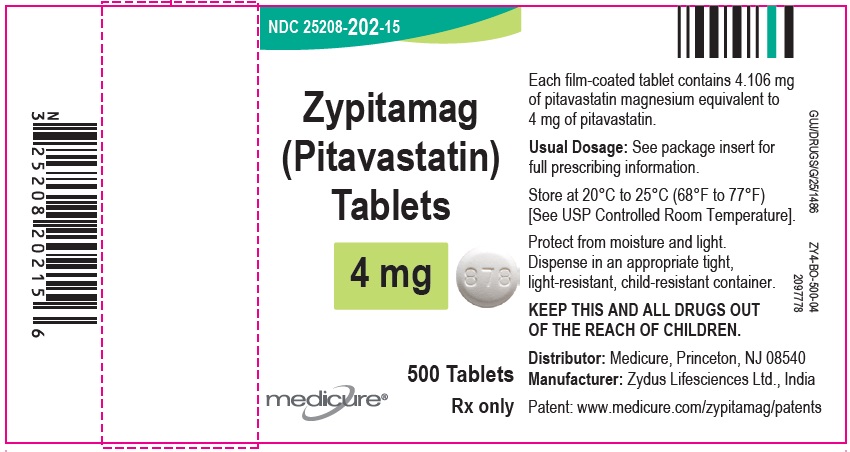 DRUG LABEL: ZYPITAMAG
NDC: 25208-201 | Form: TABLET, FILM COATED
Manufacturer: Medicure International Inc
Category: prescription | Type: HUMAN PRESCRIPTION DRUG LABEL
Date: 20251203

ACTIVE INGREDIENTS: PITAVASTATIN 2 mg/1 1
INACTIVE INGREDIENTS: CALCIUM CARBONATE; CROSPOVIDONE; HYPROMELLOSE, UNSPECIFIED; LACTOSE MONOHYDRATE; MAGNESIUM STEARATE; POLYETHYLENE GLYCOL, UNSPECIFIED; SODIUM CARBONATE; TALC; TITANIUM DIOXIDE

HIGHLIGHTS OF PRESCRIBING INFORMATION

These highlights do not include all the information needed to use ZYPITAMAG® safely and effectively. See full prescribing information for ZYPITAMAG.
ZYPITAMAG (pitavastatin) tablets, for oral use
Initial U.S. Approval: 2009

1 INDICATIONS AND USAGE

ZYPITAMAG is a HMG-CoA reductase inhibitor (statin) indicated as an adjunct to diet to reduce low-density lipoprotein cholesterol (LDL-C) in adults with primary hyperlipidemia (1).

2 DOSAGE AND ADMINISTRATION

- Take orally once daily with or without food at the same time each day. (2.1).
- For patients requiring a high-intensity statin or are unable to achieve their LDL-C goal receiving ZYPITAMAG 4 mg daily, prescribe alternative LDL-C-lowering treatment. (2.1)
- Assess LDL-C when clinically appropriate, as early as 4 weeks after initiation of ZYPITAMAG, and adjust the dosage if necessary. (2.1)
- Recommended dosage is 2 mg to 4 mg once daily. Maximum recommended dosage is 4 mg once daily. (2.2)
- Recommended starting dosage for patients with moderate and severe renal impairment and end-stage renal disease on hemodialysis is 1 mg once daily. ZYPITAMAG is not available in a 1 mg dose; use an alternative formulation of pitavastatin. Maximum recommended dosage is 2 mg once daily. (2.3)
- See full prescribing information for ZYPITAMAG dosage modifications due to drug interactions. (2.4)

3 DOSAGE FORMS AND STRENGTHS

- Tablets: 2 mg and 4 mg (3)

4 CONTRAINDICATIONS

- Cyclosporine (4, 7)
- Active liver failure or decompensated cirrhosis (4, 5.3)
- Hypersensitivity to pitavastatin or any excipients in ZYPITAMAG (4)

5 WARNINGS AND PRECAUTIONS

- Myopathy and Rhabdomyolysis: Risk factors include age 65 or greater, uncontrolled hypothyroidism, renal impairment, concomitant use with certain other drugs, and higher ZYPITAMAG dosage. Discontinue ZYPITAMAG if markedly elevated CK levels occur or myopathy is diagnosed or suspected. Temporarily discontinue ZYPITAMAG in patients experiencing an acute or serious condition at high risk of developing renal failure secondary to rhabdomyolysis. Inform patients of the risk of myopathy and rhabdomyolysis when starting or increasing the ZYPITAMAG dosage. Instruct patients to promptly report unexplained muscle pain, tenderness or weakness particularly if accompanied by malaise or fever (5.1, 7, 8.5, 8.6).
- Immune-Mediated Necrotizing Myopathy (IMNM): Rare reports of IMNM, an autoimmune myopathy, have been reported. Discontinue ZYPITAMAG if IMNM is suspected. (5.2).
- Hepatic Dysfunction: Increases in serum transaminases have occurred, some persistent. Rare reports of fatal and non-fatal hepatic failure have occurred. Consider testing liver enzyme before initiating therapy and as clinically indicated thereafter. If serious hepatic injury with clinical symptoms and/or hyperbilirubinemia or jaundice occurs, promptly discontinue ZYPITAMAG. (5.3)

6 ADVERSE REACTIONS

The most frequent adverse reactions (rate ≥ 2%) were myalgia, constipation, diarrhea, back pain, and pain in extremity. (6)

To report SUSPECTED ADVERSE REACTIONS, contact Medicure at 1-800-509-0544 or FDA at 1-800-FDA-1088 or www.fda.gov/medwatch.

7 DRUG INTERACTIONS

See full prescribing information for details regarding concomitant use of ZYPITAMAG with other drugs that increase the risk of myopathy and rhabdomyolysis. (2.4, 7).

8 USE IN SPECIFIC POPULATIONS

- Pregnancy: May cause fetal harm (8.1)
- Lactation: Breastfeeding not recommended during treatment with ZYPITAMAG (8.2)

Pediatric use information is approved for Kowa Co Ltd’s LIVALO (pitavastatin) tablets. However, due to Kowa Co Ltd’s marketing exclusivity rights, this drug product is not labeled with that information.

FULL PRESCRIBING INFORMATION

1 INDICATIONS AND USAGE

ZYPITAMAG is indicated as an adjunct to diet to reduce low-density lipoprotein cholesterol (LDL-C) in adults with primary hyperlipidemia.

Pediatric use information is approved for Kowa Co Ltd LIVALO (pitavastatin) tablets. However, due to Kowa Co Ltd marketing exclusivity rights, this drug product is not labeled with that information.

2 DOSAGE AND ADMINISTRATION

2.1 Important Dosage and Administration Information

- Take ZYPITAMAG orally once daily with or without food at the same time each day.
- For patients that require a high-intensity statin or are unable to achieve their LDL-C goal receiving ZYPITAMAG 4 mg daily, prescribe alternative LDL-C-lowering treatment.
- Assess LDL-C when clinically appropriate, as early as 4 weeks after initiating ZYPITAMAG, and adjust the dosage if necessary.

2.2 Recommended Dosage for Adults

- The recommended dosage range of ZYPITAMAG is 2 mg to 4 mg daily.
- The maximum recommended dosage is ZYPITAMAG 4 mg once daily.

2.3 Recommended Dosage in Patients with Renal Impairment

- The recommended starting dosage for patients with moderate and severe renal impairment (estimated glomerular filtration rate 30 – 59 mL/minute/1.73 m^2 and 15 – 29 mL/minute/1.73 m^2, respectively) and patients with end-stage renal disease receiving hemodialysis is pitavastatin 1 mg once daily. ZYPITAMAG is not available in a 1 mg dose; use an alternative formulation of pitavastatin for the 1 mg dose. The maximum recommended dose for these patients is ZYPITAMAG 2 mg once daily [see Use in Specific Populations (8.6)].
- There are no dosage adjustment recommendations for patients with mild renal impairment.

2.4 Dosage Adjustments Due to Drug Interactions

- In patients taking erythromycin, do not exceed pitavastatin 1 mg once daily [see Drug Interactions (7)]. ZYPITAMAG is not available in a 1 mg dose; use an alternative formulation of pitavastatin for the 1 mg dose.
- In patients taking rifampin, do not exceed ZYPITAMAG 2 mg once daily [see Drug Interactions (7)].

Pediatric use information is approved for Kowa Co Ltd’s LIVALO (pitavastatin) tablets. However, due to Kowa Co Ltd’s marketing exclusivity rights, this drug product is not labeled with that information.

3 DOSAGE FORMS AND STRENGTHS

DOSAGE FORMS AND STRENGTHS

Tablets:

- 2 mg: White to off-white, beveled-edge, round-shaped tablets debossed with “877” on one side and plain on the other side.
- 4 mg: White to off-white, beveled-edge, round-shaped tablets debossed with “878” on one side and plain on the other side.

4 CONTRAINDICATIONS

ZYPITAMAG is contraindicated in the following conditions:

- Concomitant use of cyclosporine [see Drug Interactions (7)].
- Acute liver failure or decompensated cirrhosis [see Warnings and Precautions (5.3)]
- Hypersensitivity to pitavastatin or any excipients in ZYPITAMAG. Hypersensitivity reactions including angioedema, rash, pruritus, and urticaria have been reported with pitavastatin [see Adverse Reactions (6)].

5 WARNINGS AND PRECAUTIONS

5.1 Myopathy and Rhabdomyolysis

ZYPITAMAG may cause myopathy (muscle pain, tenderness, or weakness associated with elevated creatine kinase [CK]) and rhabdomyolysis. Acute kidney injury secondary to myoglobinuria and rare fatalities have occurred as a result of rhabdomyolysis in patients treated with statins, including pitavastatin.

Risk Factors for Myopathy
Risk factors for myopathy include age 65 years or greater, uncontrolled hypothyroidism, renal impairment, concomitant use of certain drugs (including other lipid-lowering therapies), and higher ZYPITAMAG dosage [see Dosage and Administration (2.2), Drug Interactions (7), and Use in Specific Populations (8.5, 8.6)].

Dosages of pitavastatin greater than 4 mg once daily were associated with an increased risk for severe myopathy in premarketing clinical studies. The maximum recommended dose of ZYPITAMAG is 4 mg once daily.

Steps to Prevent or Reduce the Risk of Myopathy and Rhabdomyolysis
ZYPITAMAG is contraindicated in patients taking cyclosporine and not recommended in patients taking gemfibrozil [see Contraindications (4) and Drug Interactions (7)]. There are pitavastatin dosage restrictions for patients taking erythromycin or rifampin [see Dosage and Administration (2.4)]. The following drugs when used concomitantly with ZYPITAMAG may also increase the risk of myopathy and rhabdomyolysis: lipid-modifying dosages of niacin (>1 grams/day), fibrates, and colchicine [see Drug Interactions (7)].

Discontinue ZYPITAMAG if markedly elevated CK levels occur or if myopathy is either diagnosed or suspected. Muscle symptoms and CK elevations may resolve if ZYPITAMAG is discontinued. Temporarily discontinue ZYPITAMAG in patients experiencing an acute or serious condition at high risk of developing renal failure secondary to rhabdomyolysis (e.g., sepsis; shock; severe hypovolemia; major surgery; trauma; severe metabolic, endocrine, or electrolyte disorders; or uncontrolled epilepsy).

Inform patients of the risk of myopathy and rhabdomyolysis when starting or increasing the ZYPITAMAG dosage. Instruct patients to promptly report any unexplained muscle pain, tenderness or weakness, particularly if accompanied by malaise or fever.

5.2 Immune-Mediated Necrotizing Myopathy

There have been rare reports of immune-mediated necrotizing myopathy (IMNM), an autoimmune myopathy, associated with statin use, including reports of recurrence when the same or a different statin was administered. IMNM is characterized by proximal muscle weakness and elevated serum creatine kinase that persist despite discontinuation of statin treatment; positive anti-HMG CoA reductase antibody; muscle biopsy showing necrotizing myopathy; and improvement with immunosuppressive agents. Additional neuromuscular and serologic testing may be necessary. Treatment with immunosuppressive agents may be required. Discontinue ZYPITAMAG if IMNM is suspected.

5.3 Hepatic Dysfunction

Increases in serum transaminases have been reported with ZYPITAMAG [see Adverse Reactions (6)]. In most cases, these changes appeared soon after initiation, were transient, were not accompanied by symptoms, and resolved or improved on continued therapy or after a brief interruption in therapy. There have been rare postmarketing reports of fatal and non-fatal hepatic failure in patients taking statins, including pitavastatin.

Patients who consume substantial quantities of alcohol and/or have a history of liver disease may be at increased risk for hepatic injury.

Consider liver enzyme testing before the initiation of ZYPITAMAG and when clinically indicated thereafter. ZYPITAMAG is contraindicated in patients with acute liver failure or decompensated cirrhosis [see Contraindications (4)]. If serious hepatic injury with clinical symptoms and/or hyperbilirubinemia or jaundice occurs, promptly discontinue ZYPITAMAG.

5.4 Increases in HbA1c and Fasting Serum Glucose Levels

Increases in HbA1c and fasting serum glucose levels have been reported with statins, including pitavastatin. Optimize lifestyle measures, including regular exercise, maintaining a healthy body weight, and making healthy food choices.

6 ADVERSE REACTIONS

The following serious adverse reactions are discussed in other sections of the labeling:

- Myopathy and Rhabdomyolysis [see Warnings and Precautions (5.1)].
- Immune-Mediated Necrotizing Myopathy [see Warnings and Precautions (5.2)]
- Hepatic Dysfunction [see Warnings and Precautions (5.3)]
- Increases in HbA1c and Fasting Serum Glucose Levels [see Warnings and Precautions (5.4)].

6.1 Clinical Studies Experience

Because clinical studies are conducted under widely varying conditions, adverse reaction rates observed in the clinical studies of one drug cannot be directly compared to rates in the clinical studies of another drug and may not reflect the rates observed in practice.

Adverse Reactions in Adults with Primary Hyperlipidemia
In 10 controlled clinical studies and 4 subsequent open-label extension studies, 3,291 adult patients with primary hyperlipidemia were administered pitavastatin 1 mg to 4 mg daily. The mean continuous exposure of pitavastatin (1 mg to 4 mg) was 36.7 weeks (median 51.1 weeks). The mean age of the patients was 60.9 years (range; 18 years – 89 years) and 52% females. Approximately 93% of the patients were White 7% were Asian/Indian, 0.2% were African American and 0.3% were Hispanic and other.

In controlled clinical studies and their open-label extensions, 3.9% (1 mg), 3.3% (2 mg), and 3.7% (4 mg) of pitavastatin-treated patients were discontinued due to adverse reactions. The most common adverse reactions that led to treatment discontinuation were: elevated creatine phosphokinase (0.6% on 4 mg) and myalgia (0.5% on 4 mg).

Adverse reactions reported in ≥ 2% of patients in controlled clinical studies and at a rate greater than or equal to placebo are shown in Table 1. These studies had treatment duration of up to 12 weeks.

Table 1. Adverse Reactions (≥ 2% and ≥ placebo) in Adult Patients with Primary Hyperlipidemia and Mixed Dyslipidemia in Studies up to 12 Weeks
Adverse Reactions | Placebo N=208; % | Pitavastatin 1 mg N=309; % | Pitavastatin 2 mg N=951; % | Pitavastatin 4 mg N=1540; %
Myalgia | 1.4 | 1.9 | 2.8 | 3.1
Constipation | 1.9 | 3.6 | 1.5 | 2.2
Diarrhea | 1.9 | 2.6 | 1.5 | 1.9
Back pain | 2.9 | 3.9 | 1.8 | 1.4
Pain in extremity | 1.9 | 2.3 | 0.6 | 0.9

Other adverse reactions reported from clinical studies were arthralgia, headache, influenza, and nasopharyngitis.

Hypersensitivity reactions including rash, pruritus, and urticaria have been reported with pitavastatin.

The following laboratory abnormalities have been reported: elevated creatine phosphokinase, transaminases, alkaline phosphatase, bilirubin, and glucose.

Adverse Reactions in Adult HIV-Infected Patients with Dyslipidemia

In a double-blind, randomized, controlled, 52-week trial, 252 HIV-infected patients with dyslipidemia were treated with either pitavastatin 4 mg once daily (n=126) or another statin (n=126). All patients were taking antiretroviral therapy (excluding darunavir) and had HIV-1 RNA less than 200 copies/mL and CD4 count greater than 200 cell/μL for at least 3 months prior to randomization. The safety profile of pitavastatin was generally consistent with that observed in the clinical trials described above. One patient (0.8%) treated with pitavastatin had a peak creatine phosphokinase value exceeding 10 times the upper limit of normal (ULN), which resolved spontaneously. Four patients (3%) treated with pitavastatin had at least one ALT value exceeding 3 times but less than 5 times the ULN, none of which led to drug discontinuation. Virologic failure was reported for four patients (3%) treated with pitavastatin, defined as a confirmed measurement of HIV-1 RNA exceeding 200 copies/mL that was also more than a 2-fold increase from baseline.

Pediatric use information is approved for Kowa Co Ltd’s LIVALO (pitavastatin) tablets. However, due to Kowa Co Ltd’s marketing exclusivity rights, this drug product is not labeled with that information.

6.2 Postmarketing Experience

The following adverse reactions have been identified during post-approval use of pitavastatin. Because these reactions are reported voluntarily from a population of uncertain size, it is not always possible to reliably estimate their frequency or establish a causal relationship to drug exposure.

Gastrointestinal disorders: abdominal discomfort, abdominal pain, dyspepsia, nausea

General disorders: asthenia, fatigue, malaise, dizziness

Hepatobiliary disorders: hepatitis, jaundice, fatal and non-fatal hepatic failure

Immune system disorders: angioedema, immune-mediated necrotizing myopathy associated with statin use

Metabolism and nutrition disorders: increases in HbA1c, fasting serum glucose levels

Musculoskeletal and connective tissue disorders: muscle spasms, myopathy, rhabdomyolysis

Nervous system disorders: hypoesthesia, peripheral neuropathy, rare reports of cognitive impairment (e.g., memory loss, forgetfulness, amnesia, memory impairment, confusion) associated with statin use. Cognitive impairment was generally nonserious, and reversible upon statin discontinuation, with variable times to symptom onset (1 day to years) and symptom resolution (median of 3 weeks). There have been rare reports of new-onset or exacerbation of myasthenia gravis, including ocular myasthenia, and reports of recurrence when the same or a different statin was administered.

Psychiatric disorders: insomnia, depression.

Reproductive system and breast disorders: erectile dysfunction

Respiratory, thoracic and mediastinal disorders: interstitial lung disease

Skin and subcutaneous tissue disorders: lichen planus

7 DRUG INTERACTIONS

Table 2 includes a list of drugs that increase the risk of myopathy and rhabdomyolysis when

administered concomitantly with ZYPITAMAG and instructions for preventing or managing drug
interactions [see Warnings and Precautions (5.1), Clinical Pharmacology (12.3)].

Table 2. Drug Interactions that Increase the Risk of Myopathy and Rhabdomyolysis with ZYPITAMAG
Cyclosporine
Clinical Impact: | Cyclosporine significantly increases pitavastatin exposure and increases the risk of myopathy and rhabdomyolysis.
Intervention: | Concomitant use of cyclosporine with ZYPITAMAG is contraindicated [see Contraindications (4)].
Gemfibrozil
Clinical Impact: | Gemfibrozil may cause myopathy when given alone. The risk of myopathy and rhabdomyolysis is increased with concomitant use of gemfibrozil with statins, including pitavastatin.
Intervention: | Avoid concomitant use of gemfibrozil with ZYPITAMAG.
Erythromycin
Clinical Impact: | Erythromycin significantly increases pitavastatin exposure and increases the risk of myopathy and rhabdomyolysis.
Intervention: | In patients taking erythromycin, do not exceed ZYPITAMAG 1 mg once daily [see Dosage and Administration (2.4)].
Rifampin
Clinical Impact: | Rifampin significantly increases peak pitavastatin exposure and increases the risk of myopathy and rhabdomyolysis.
Intervention: | In patients taking rifampin, do not exceed ZYPITAMAG 2 mg once daily [see Dosage and Administration (2.4)].
Fibrates
Clinical Impact: | Fibrates may cause myopathy when given alone. The risk of myopathy and rhabdomyolysis is increased with concomitant use of fibrates with statins, including pitavastatin.
Intervention: | Consider if the benefit of using fibrates concomitantly with ZYPITAMAG outweighs the increased risk of myopathy and rhabdomyolysis.
Niacin
Clinical Impact: | The risk of myopathy and rhabdomyolysis may be increased with concomitant use of lipid-modifying doses (1 g/day) of niacin with pitavastatin.
Intervention: | Consider if the benefit of using lipid-modifying doses (>1 g/day) of niacin concomitantly with ZYPITAMAG outweighs the increased risk of myopathy and rhabdomyolysis.
Colchicine
Clinical Impact: | Cases of myopathy and rhabdomyolysis have been reported with concomitant use of colchicine with statins, including pitavastatin.
Intervention: | Consider the risk/benefit of concomitant use of colchicine with ZYPITAMAG.

8 USE IN SPECIFIC POPULATIONS

8.1 Pregnancy

Risk Summary

Discontinue ZYPITAMAG when pregnancy is recognized. Alternatively, consider the ongoing therapeutic needs of the individual patient.

ZYPITAMAG decreases synthesis of cholesterol and possibly other biologically active substances derived from cholesterol; therefore, ZYPITAMAG may cause fetal harm when administered to pregnant patients based on the mechanism of action [see Clinical Pharmacology (12.1)]. In addition, treatment of hyperlipidemia is not generally necessary during pregnancy. Atherosclerosis is a chronic process and the discontinuation of
lipid-lowering drugs during pregnancy should have little impact on the outcome of long-term therapy of primary hyperlipidemia for most patients.

Available data from case series and prospective and retrospective observational cohort studies over decades of use with statins in pregnant women have not identified a drug-associated risk of major congenital malformations. Published data from prospective and retrospective observational cohort studies with statin use in pregnant women are insufficient to determine if there is a drug-associated risk of miscarriage (see Data).

In animal reproduction studies, no embryo-fetal toxicity or congenital malformations were observed in pregnant rats or rabbits orally administered pitavastatin during the period of organogenesis at doses that resulted in
22 and 4 times, respectively, the human exposure at the maximum recommended human dose (MRHD) of 4 mg, based on AUC (see Data).

The estimated background risk of major birth defects and miscarriage for the indicated population is unknown. In the U.S. general population, the estimated background risk of major birth defects and miscarriage in clinically recognized pregnancies is 2% to 4% and 15% to 20%, respectively.

Data
Human Data
A Medicaid cohort linkage study of 1152 statin-exposed pregnant women compared to 886,996 controls did not find a significant teratogenic effect from maternal use of statins in the first trimester of pregnancy, after adjusting for potential confounders – including maternal age, diabetes mellitus, hypertension, obesity, and alcohol and tobacco use -using propensity score-based methods. The relative risk of congenital malformations between the group with statin use and the group with no statin use in the first trimester was 1.07 (95% confidence interval 0.85 to 1.37) after controlling for confounders, particularly pre-existing diabetes mellitus.

There were also no statistically significant increases in any of the organ-specific malformations assessed after accounting for confounders. In the majority of pregnancies, statin treatment was initiated prior to pregnancy and was discontinued at some point in the first trimester when pregnancy was identified. Study limitations include reliance on physician coding to define the presence of a malformation, lack of control for certain confounders such as body mass index, use of prescription dispensing as verification for use of a statin, and a lack of information on non-live births.

Animal Data
Embryo-fetal developmental studies were conducted in pregnant rats administered 3 mg/kg/day, 10 mg/kg/day, 30 mg/kg/day pitavastatin by oral gavage during organogenesis (gestation day 7-17). No adverse effects were observed at 3 mg/kg/day, systemic exposures 22 times human systemic exposure at 4 mg/day based on AUC.

Embryo-fetal developmental studies were conducted in pregnant rabbits administered 0.1 mg/kg/day, 0.3 mg/kg/day, 1 mg/kg/day pitavastatin by oral gavage during the period of fetal organogenesis (gestation day 6-18). Maternal toxicity consisting of reduced body weight and abortion was observed at all doses tested
(4 times human systemic exposure at 4 mg/day based on AUC).

In perinatal/postnatal studies in pregnant rats given oral gavage doses of pitavastatin at 0.1 mg/kg/day, 0.3 mg/kg/day, 1 mg/kg/day, 3 mg/kg/day, 10 mg/kg/day, 30 mg/kg/day from organogenesis through weaning (gestation day 17 to lactation day 21), maternal toxicity consisting of mortality at ≥ 0.3 mg/kg/day and impaired lactation at all doses contributed to the decreased survival of neonates in all dose groups (0.1 mg/kg/day represents approximately 1 time human systemic exposure at 4 mg/day dose based on AUC).

Reproductive toxicity studies have shown that pitavastatin crosses the placenta in rats and is found in fetal tissues at ≤ 36% of maternal plasma concentrations following a single dose of 1 mg/kg/day during gestation (at the end of organogenesis).

8.2 Lactation

Risk Summary
There is no available information about the presence of pitavastatin in human or animal milk, the effects of the drug on the breastfed infant, or the effects of the drug on milk production. However, it has been shown that another drug in this class passes into human milk. Statins, including pitavastatin, decrease cholesterol synthesis and possibly the synthesis of other biologically active substances derived from cholesterol and may cause harm to the breastfed infant.

Because of the potential for serious adverse reactions in a breastfed infant, based upon the mechanism of action, advise patients that breastfeeding is not recommended during treatment with ZYPITAMAG [see Use in Specific Populations (8.1), Clinical Pharmacology (12.1)].

8.4 Pediatric Use

The safety and effectiveness of ZYPITAMAG in pediatric patients have not been established.

Pediatric use information is approved for Kowa Co Ltd LIVALO (pitavastatin) tablets. However, due to Kowa Co Ltd marketing exclusivity rights, this drug product is not labeled with that information.

8.5 Geriatric Use

In controlled clinical studies, 1,209 (43%) patients were 65 years and older. No overall differences in safety or effectiveness were observed between these patients and younger patients.

Advanced age (≥ 65 years) is a risk factor for pitavastatin-associated myopathy and rhabdomyolysis. Dose selection for a geriatric patient should be cautious, recognizing the greater frequency of decreased hepatic, renal, or cardiac function, and of concomitant disease or other drug therapy and the higher risk of myopathy. Monitor geriatric patients receiving ZYPITAG for the increased risk of myopathy [see Warnings and Precautions (5.1)].

8.6 Renal Impairment

Renal impairment is a risk factor for myopathy and rhabdomyolysis. Monitor all patients with renal impairment for development of myopathy. Due to the risk of myopathy, a dosage modification of ZYPITAMAG is recommended for patients with moderate and severe renal impairment (estimated glomerular filtration rate 30 – 59 mL/min/1.73 m^2 and 15 – 29 mL/min/1.73 m^2, respectively), as well as end-stage renal disease receiving hemodialysis [see Dosage and Administration (2.3), Warnings and Precautions (5.1), Clinical Pharmacology (12.3)].

8.7 Hepatic Impairment

ZYPITAMAG is contraindicated in patients with active liver failure or decompensated cirrhosis[see Contraindications (4), Warnings and Precautions (5.3)].

10 OVERDOSAGE

No specific treatment for pitavastatin overdose is known. Contact Poison Control (1-800-222-1222) for latest recommendations. Hemodialysis is unlikely to be of benefit due to high protein binding ratio of pitavastatin.

11 DESCRIPTION

ZYPITAMAG (pitavastatin) tablets for oral use is an HMG-CoA reductase inhibitor.

The chemical name for pitavastatin is (3R,5S)-7-[2-Cyclopropyl-4-(4-fluorophenyl) quinoline-3-yl]3,5-dihydroxy-6(E)-heptanoic acid hemi magnesium. The structural formula is:

The molecular formula for pitavastatin is C50H46MgF2N2O8 and the molecular weight is 865.21. Pitavastatin is a white to off-white powder. It is freely soluble in acetone, ethyl acetate; soluble in dimethylsulfoxide and insoluble in dichloromethane and isopropyl alcohol. Pitavastatin is hygroscopic and slightly unstable in light.

Each film-coated tablet of ZYPITAMAG contains 2.053 mg or 4.106 mg of pitavastatin magnesium, which is equivalent to 2 mg or 4 mg, respectively of free base and the following inactive ingredients: calcium carbonate, crospovidone, hypromellose, lactose monohydrate, magnesium stearate and sodium carbonate anhydrous and film-coating containing the following inactive ingredients: hypromellose, polyethylene glycol, talc and titanium dioxide.

12 CLINICAL PHARMACOLOGY

12.1 Mechanism of Action

Pitavastatin is an inhibitor of 3-hydroxy-3-methylglutaryl-coenzyme A (HMG-CoA) reductase, the enzyme that catalyzes the conversion of HMG-CoA to mevalonate, a rate-limiting step in the biosynthetic pathway for cholesterol. As a result, the expression of LDL-receptors followed by the uptake of LDL from blood to liver is accelerated and then the plasma TC decreases. Sustained inhibition of cholesterol synthesis in the liver also decreases levels of very low density lipoproteins.

12.2 Pharmacodynamics

Cardiac Electrophysiology
In a randomized, double-blind, placebo-controlled, 4-way parallel, active-comparator study with moxifloxacin in 174 healthy participants, pitavastatin was not associated with clinically meaningful prolongation of the QTc interval or heart rate at daily doses up to 16 mg (4 times the recommended maximum dose of 4 mg daily).

12.3 Pharmacokinetics

Absorption

Pitavastatin peak plasma concentrations are achieved about 1 hour after oral administration. Both Cmax and AUC0-inf increased in an approximately dose-proportional manner for single pitavastatin doses from 1 mg to 24 mg once daily. The absolute bioavailability of pitavastatin oral solution is 51%. The Cmax and AUC of pitavastatin did not differ following evening or morning drug administration. In healthy volunteers receiving 4 mg pitavastatin, the percent change from baseline for LDL-C following evening dosing was slightly greater than that following morning dosing. Pitavastatin was absorbed in the small intestine but very little in the colon.

Effect of Food
Administration of pitavastatin with a high fat meal (50% fat content) decreases pitavastatin Cmax by 43% but does not significantly reduce pitavastatin AUC.

Distribution
Pitavastatin is more than 99% protein bound in human plasma, mainly to albumin and alpha 1-acid glycoprotein, and the mean volume of distribution is approximately 148 L.

Elimination
Metabolism
The principal route of pitavastatin metabolism is glucuronidation via liver uridine 5'-diphosphate glucuronosyltransferase (UGT) with subsequent formation of pitavastatin lactone. There is only minimal metabolism by the cytochrome P450 system. Pitavastatin is marginally metabolized by CYP2C9 and to a lesser extent by CYP2C8. The major metabolite in human plasma is the lactone which is formed via an ester-type pitavastatin glucuronide conjugate by UGTs (UGT1A3 and UGT2B7).

Excretion
A mean of 15% of radioactivity of orally administered, single 32 mg ^14C-labeled pitavastatin dose was excreted in urine, whereas a mean of 79% of the dose was excreted in feces within 7 days. The mean plasma elimination half-life is approximately 12 hours.

Specific Populations
Geriatric Patients
In a pharmacokinetic study which compared healthy young and geriatric (≥65 years) volunteers, pitavastatin Cmax and AUC were 10 and 30% higher, respectively, in the geriatric patients [see Use in Specific Populations (8.5)].

Pediatric Patients
Pediatric use information is approved for Kowa Co Ltd LIVALO (pitavastatin) tablets. However, due to Kowa Co Ltd marketing exclusivity rights, this drug product is not labeled with that information.

Male and Female Patients
In a pharmacokinetic study, which compared healthy male and female volunteers, pitavastatin Cmax and AUC were 60 and 54% higher, respectively in females.

Racial or Ethnic Groups
In pharmacokinetic studies pitavastatin Cmax and AUC were 21 and 5% lower, respectively in Black or African American healthy volunteers compared with those of White healthy volunteers. In pharmacokinetic comparison between Whitevolunteers and Japanese volunteers, there were no significant differences in Cmax and AUC.

Patients with Renal Impairment

In adult patients with moderate renal impairment (estimated glomerular filtration rate of 30 mL/min/1.73 m^2 to 59 mL/min/1.73 m^2) and end stage renal disease receiving hemodialysis, pitavastatin AUC0-inf is 102% and 86% higher than those of healthy volunteers, respectively, while pitavastatin Cmax is 60% and 40% higher than those of healthy volunteers, respectively. Patients received hemodialysis immediately before pitavastatin dosing and did not undergo hemodialysis during the pharmacokinetic study. Hemodialysis patients have 33% and 36% increases in the mean unbound fraction of pitavastatin as compared to healthy volunteers and patients with moderate renal impairment, respectively [see Use in Specific Populations (8.6)].

In another pharmacokinetic study, adult patients with severe renal impairment (estimated glomerular filtration rate 15 mL/min/1.73 m^2 to 29 mL/min/1.73 m^2) not receiving hemodialysis were administered a single dose of pitavastatin 4 mg. The AUC0-inf and the Cmax were 36% and 18% higher, respectively, compared with those of healthy volunteers. For both patients with severe renal impairment and healthy volunteers, the mean percentage of protein-unbound pitavastatin was approximately 0.6% [see Use in Specific Populations (8.6)].

The effect of mild renal impairment on pitavastatin exposure has not been studied.

Patients with Hepatic Impairment
The disposition of pitavastatin was compared in healthy volunteers and patients with various degrees of hepatic impairment. Pitavastatin Cmax and AUCinf in patients with moderate hepatic impairment (Child-Pugh B disease) was 2.7-fold and 3.8-fold higher, respectively as compared to health volunteers. In patients with mild hepatic impairment (Child-Pugh A disease), pitavastatin Cmax and AUCinf were 30% and 60% higher as compared to healthy volunteers. Mean pitavastatin half-life for moderate hepatic impairment, mild hepatic impairment, and healthy were 15, 10, and 8 hours, respectively [see Contraindications (4), Warnings and Precautions (5.3)].

Drug Interaction Studies

Warfarin
The steady-state pharmacodynamics (international normalized ratio [INR] and prothrombin time [PT]) and pharmacokinetics of warfarin in healthy volunteers were unaffected by the coadministration of pitavastatin 4 mg daily.

Table 3 presents the effect of coadministered drugs on pitavastatin systemic exposure:

Table 3 Effect of Coadministered Drugs on Pitavastatin Systemic Exposure
Coadministered drug | Dosage regimen | Change in AUC* | Change in C max*
Cyclosporine | Pitavastatin 2 mg QD for 6 days + cyclosporine 2 mg/kg on Day 6 | ↑ 4.6 fold † | ↑ 6.6 fold †
Erythromycin | Pitavastatin 4 mg single dose on Day 4 + erythromycin 500 mg 4 times daily for 6 days | ↑ 2.8 fold † | ↑ 3.6 fold †
Rifampin | Pitavastatin 4 mg QD + rifampin 600 mg QD for 5 days | ↑ 29% | ↑ 2 fold
Atazanavir | Pitavastatin 4 mg QD + atazanavir 300 mg daily for 5 days | ↑ 31% | ↑ 60%
Darunavir/Ritonavir | Pitavastatin 4 mg QD on Days 1 to 5 and 12 to 16 + darunavir/ritonavir 800 mg/100 mg QD on Days 6 to 16 | ↓ 26% | ↓ 4%
Lopinavir/Ritonavir | Pitavastatin 4 mg QD on Days 1 to 5 and 20 to 24 + lopinavir/ritonavir 400 mg/100 mg BID on Days 9 to 24 | ↓ 20% | ↓ 4%
Gemfibrozil | Pitavastatin 4 mg QD + gemfibrozil 600 mg BID for 7 days | ↑ 45% | ↑ 31%
Fenofibrate | Pitavastatin 4 mg QD + fenofibrate 160 mg QD for 7 days | ↑ 18% | ↑ 11%
Ezetimibe | Pitavastatin 2 mg QD + ezetimibe 10 mg for 7 days | ↓ 2% | ↓ 0.2%
Enalapril | Pitavastatin 4 mg QD + enalapril 20 mg daily for 5 days | ↑ 6% | ↓ 7%
Digoxin | Pitavastatin 4 mg QD + digoxin 0.25 mg for 7 days | ↑ 4% | ↓ 9%
Diltiazem LA | Pitavastatin 4 mg QD on Days 1 to 5 and 11 to 15 and diltiazem LA 240 mg on Days 6 to 15 | ↑ 10% | ↑ 15%
Grapefruit Juice | Pitavastatin 2 mg single dose on Day 3 + grapefruit juice for 4 days | ↑ 15% | ↓ 12%
Itraconazole | Pitavastatin 4 mg single dose on Day 4 + itraconazole 200 mg daily for 5 days | ↓ 23% | ↓ 22%
*Data presented as x-fold change represent the ratio between coadministration and pitavastatin alone (i.e., 1-fold = no change). Data presented as % change represent % difference relative to pitavastatin alone (i.e., 0% = no change).
† Considered clinically significant [see Dosage and Administration (2) and Drug Interactions (7)]
BID = twice daily; QD = once daily; LA = Long Acting

Table 4 presents the effect of pitavastatin coadministration on systemic exposure of other drugs:

Table 4 Effect of Pitavastatin Coadministration on Systemic Exposure to Other Drugs
Coadministered drug | Dose regimen |  | Change in AUC* | Change in C max *
Atazanavir | Pitavastatin 4 mg QD + atazanavir 300 mg daily for 5 days |  | ↑ 6% | ↑ 13%
Darunavir | Pitavastatin 4 mg QD on Days 1 to 5 and 12 to 16 + darunavir/ritonavir 800 mg/100 mg QD on Days 6 to 16 |  | ↑ 3% | ↑ 6%
Lopinavir | Pitavastatin 4 mg QD on Days 1 to 5 and 20 to 24 + lopinavir/ritonavir 400 mg/100 mg BID on Days 9 to 24 |  | ↓ 9% | ↓ 7%
Ritonavir | Pitavastatin 4 mg QD on Days 1 to 5 and 20 to 24 + lopinavir/ritonavir 400 mg/100 mg BID on Days 9 to 24 |  | ↓ 11% | ↓ 11%
Ritonavir | Pitavastatin 4 mg QD on Days 1 to 5 and 12 to 16 + darunavir/ritonavir 800 mg/100 mg QD on Days 6 to 16 |  | ↑ 8% | ↑ 2%
Enalapril | Pitavastatin 4 mg QD + enalapril 20 mg daily for 5 days | Enalapril | ↑ 12% | ↑ 12%
Enalapril | Pitavastatin 4 mg QD + enalapril 20 mg daily for 5 days | Enalaprilat | ↓ 1% | ↓ 1%
Warfarin | Individualized maintenance dose of warfarin (2 to 7 mg) for 8 days + pitavastatin 4 mg QD for 9 days | R-warfarin | ↑ 7% | ↑ 3%
Warfarin | Individualized maintenance dose of warfarin (2 to 7 mg) for 8 days + pitavastatin 4 mg QD for 9 days | S-warfarin | ↑ 6% | ↑ 3%
Ezetimibe | Pitavastatin 2 mg QD + ezetimibe 10 mg for 7 days |  | ↑ 9% | ↑ 2%
Digoxin | Pitavastatin 4 mg QD + digoxin 0.25 mg for 7 days |  | ↓ 3% | ↓ 4%
Diltiazem LA | Pitavastatin 4 mg QD on Days 1 to 5 and 11 to 15 and diltiazem LA 240 mg on Days 6 to 15 |  | ↓ 2% | ↓ 7%
Rifampin | Pitavastatin 4 mg QD + rifampin 600 mg QD for 5 days |  | ↓ 15% | ↓ 18%
*Data presented as % change represent % difference relative to the investigated drug alone (i.e., 0% = no change).
BID = twice daily; QD = once daily; LA = Long Acting

13 NONCLINICAL TOXICOLOGY

13.1 Carcinogenesis, Mutagenesis, Impairment of Fertility

In a 92 week carcinogenicity study in mice given pitavastatin, at the maximum tolerated dose of 75 mg/kg/day with systemic maximum exposures (AUC) 26 times the clinical maximum exposure at 4 mg daily, there was an absence of drug-related tumors.

In a 92 week carcinogenicity study in rats given pitavastatin at 1 mg/kg/day, 5 mg/kg/day, 25 mg/kg/day by oral gavage there was a significant increase in the incidence of thyroid follicular cell tumors at 25 mg/kg/day, which represents 295 times human systemic exposures based on AUC at the 4 mg daily maximum human dose.

In a 26 week transgenic mouse (Tg rasH2) carcinogenicity study where animals were given pitavastatin at 30 mg/kg/day, 75 mg/kg/day, and 150 mg/kg/day by oral gavage, no clinically significant tumors were observed.

Pitavastatin was not mutagenic in the Ames test with Salmonella typhimurium and Escherichia coli with and without metabolic activation, the micronucleus test following a single administration in mice and multiple administrations in rats, the unscheduled DNA synthesis test in rats, and a Comet assay in mice. In the chromosomal aberration test, clastogenicity was observed at the highest doses tested which also elicited high levels of cytotoxicity.

Pitavastatin had no adverse effects on male and female rat fertility at oral doses of 10 mg/kg/day and 30 mg/kg/day, respectively, at systemic exposures 56 and 354 times clinical exposure at 4 mg daily based on AUC.

Pitavastatin treatment in rabbits resulted in mortality in males and females given 1 mg/kg/day (30 times clinical systemic exposure at 4 mg daily based on AUC) and higher during a fertility study. Although the cause of death was not determined, rabbits had gross signs of renal toxicity (kidneys whitened) indicative of possible ischemia. Lower doses (15 times human systemic exposure) did not show significant toxicity in adult males and females. However, decreased implantations, increased resorptions, and decreased viability of fetuses were observed.

14 CLINICAL STUDIES

Primary Hyperlipidemia in Adults
Study with Atorvastatin (Study 301)

Pitavastatin was compared with atorvastatin calcium tablets (referred to as atorvastatin) in a randomized, multicenter, double-blind, double-dummy, active-controlled, non-inferiority study of 817 adult patients with primary hyperlipidemia or mixed dyslipidemia. Patients entered a 6- to 8-week wash-out/dietary lead-in period and then were randomized to a 12-week treatment with either pitavastatin or atorvastatin (Table 5). Non-inferiority of pitavastatin to a given dose of atorvastatin was considered to be demonstrated if the lower bound of the 95% CI for the mean treatment difference was greater than -6% for the mean percent change in LDL-C.

Lipid results are shown in Table 5. For the percent change from baseline to endpoint in LDL-C, pitavastatin was non-inferior to atorvastatin for the two pairwise comparisons: pitavastatin 2 mg vs. atorvastatin 10 mg and pitavastatin 4 mg vs. atorvastatin 20 mg. Mean treatment differences (95% CI) were 0% (-3%, 3%) and 1% (-2%, 4%), respectively.

Table 5 Lipid Response by Dose of Pitavastatin and Atorvastatin in Adult Patients with Primary Hyperlipidemia or Mixed Dyslipidemia in Study 301 (Mean % Change from Baseline at Week 12)
Treatment | N | LDL-C | Apo-B | TC | TG | HDL-C | non-HDL-C
Pitavastatin 2 mg daily | 315 | -38 | -30 | -28 | -14 | 4 | -35
Pitavastatin 4 mg daily | 298 | -45 | -35 | -32 | -19 | 5 | -41
Atorvastatin 10 mg daily | 102 | -38 | -29 | -28 | -18 | 3 | -35
Atorvastatin 20 mg daily | 102 | -44 | -36 | -33 | -22 | 2 | -41

Study with Simvastatin (Study 302)

Pitavastatin was compared with simvastatin tablets (referred to as simvastatin) in a randomized, multicenter, double-blind, double-dummy, active-controlled, non-inferiority study of 843 adult patients with primary hyperlipidemia or mixed dyslipidemia. Patients entered a 6- to 8-week wash-out/dietary lead-in period and then were randomized to a 12-week treatment with either pitavastatin or simvastatin (Table 6). Non-inferiority of pitavastatin to a given dose of simvastatin was considered to be demonstrated if the lower bound of the 95% CI for the mean treatment difference was greater than -6% for the mean percent change in LDL-C.

Lipid results are shown in Table 6. For the percent change from baseline to endpoint in LDL-C, pitavastatin was non-inferior to simvastatin for the two pairwise comparisons: pitavastatin 2 mg vs. simvastatin 20 mg and pitavastatin 4 mg vs. simvastatin 40 mg. Mean treatment differences (95% CI) were 4% (1%, 7%) and 1% (-2%, 4%), respectively.

Table 6 Lipid Response by Dose of Pitavastatin and Simvastatin in Adult Patients with Primary Hyperlipidemia or Mixed Dyslipidemia in Study 302 (Mean % Change from Baseline at Week 12)
Treatment | N | LDL-C | Apo-B | TC | TG | HDL-C | non-HDL-C
Pitavastatin 2 mg daily | 307 | -39 | -30 | -28 | -16 | 6 | -36
Pitavastatin 4 mg daily | 319 | -44 | -35 | -32 | -17 | 6 | -41
Simvastatin 20 mg daily | 107 | -35 | -27 | -25 | -16 | 6 | -32
Simvastatin 40 mg daily | 110 | -43 | -34 | -31 | -16 | 7 | -39

Study with Pravastatin in Geriatric Patients (Study 306)

Pitavastatin was compared with pravastatin sodium tablets (referred to as pravastatin) in a randomized, multicenter, double-blind, double-dummy, parallel group, active-controlled non-inferiority study of 942 geriatric patients (≥ 65 years) with primary hyperlipidemia or mixed dyslipidemia. Patients entered a 6- to 8-week wash-out/dietary lead-in period, and then were randomized to a once daily dose of pitavastatin or pravastatin for 12 weeks (Table 7). Non-inferiority of pitavastatin to a given dose of pravastatin was assumed if the lower bound of the 95% CI for the treatment difference was greater than -6% for the mean percent change in LDL-C.

Lipid results are shown in Table 7. Pitavastatin significantly reduced LDL-C compared to pravastatin as demonstrated by the following pairwise dose comparisons: pitavastatin 1 mg vs. pravastatin 10 mg, pitavastatin 2 mg vs. pravastatin 20 mg and pitavastatin 4 mg vs. pravastatin 40 mg. Mean treatment differences (95% CI) were 9% (6%, 12%), 10% (7%, 13%) and 10% (7%, 13%), respectively.

Table 7 Lipid Response by Dose of Pitavastatin and Pravastatin in Geriatric Patients with Primary Hyperlipidemia or Mixed Dyslipidemia in Study 306 (Mean % Change from Baseline at Week 12)
Treatment | N | LDL-C | Apo-B | TC | TG | HDL-C | non-HDL-C
Pitavastatin 1 mg daily | 207 | -31 | -25 | -22 | -13 | 1 | -29
Pitavastatin 2 mg daily | 224 | -39 | -31 | -27 | -15 | 2 | -36
Pitavastatin 4 mg daily | 210 | -44 | -37 | -31 | -22 | 4 | -41
Pravastatin 10 mg daily | 103 | -22 | -17 | -15 | -5 | 0 | -20
Pravastatin 20 mg daily | 96 | -29 | -22 | -21 | -11 | -1 | -27
Pravastatin 40 mg daily | 102 | -34 | -28 | -24 | -15 | 1 | -32

Study with Simvastatin in Patients with ≥ 2 Risk Factors for Coronary Heart Disease (Study 304)

Pitavastatin was compared with simvastatin tablets (referred to as simvastatin) in a randomized, multicenter, double-blind, double-dummy, active-controlled, non-inferiority study of 351 adult patients with primary hyperlipidemia or mixed dyslipidemia with ≥ 2 risk factors for coronary heart disease. After a 6- to 8-week wash-out/dietary lead-in period, patients were randomized to a 12-week treatment with either pitavastatin or simvastatin (Table 8). Non-inferiority of pitavastatin to simvastatin was considered to be demonstrated if the lower bound of the 95% CI for the mean treatment difference was greater than -6% for the mean percent change in LDL-C.

Lipid results are shown in Table 8. Pitavastatin 4 mg was non-inferior to simvastatin 40 mg for percent change from baseline to endpoint in LDL-C. The mean treatment difference (95% CI) was 0% (-2%, 3%).

Table 8 Lipid Response by Dose of Pitavastatin and Simvastatin in Adult Patients with Primary Hyperlipidemia or Mixed Dyslipidemia with ≥ 2 Risk Factors for Coronary Heart Disease in Study 304 (Mean % Change from Baseline at Week 12)
Treatment | N | LDL-C | Apo-B | TC | TG | HDL-C | non-HDL-C
Pitavastatin 4 mg daily | 233 | -44 | -34 | -31 | -20 | 7 | -40
Simvastatin 40 mg daily | 118 | -44 | -34 | -31 | -15 | 5 | -39

Study with Atorvastatin in Patients with Type 2 Diabetes Mellitus (Study 305)

Pitavastatin was compared with atorvastatin calcium tablets (referred to as atorvastatin) in a randomized, multicenter, double-blind, double-dummy, parallel group, active-controlled, non-inferiority study of 410 adult patients with type 2 diabetes mellitus and mixed dyslipidemia. Patients entered a 6 to 8 week wash-out/dietary lead-in period and were randomized to a once daily dose of pitavastatin or atorvastatin for 12 weeks. Non-inferiority of pitavastatin was considered to be demonstrated if the lower bound of the 95% CI for the mean treatment difference was greater than -6% for the mean percent change in LDL-C.

Lipid results are shown in Table 9. The treatment difference (95% CI) for LDL-C percent change from baseline was -2% (-6.2%, 1.5%). The two treatment groups were not statistically different on LDL-C. However, the lower limit of the CI was -6.2%, slightly exceeding the -6% non-inferiority limit The study failed to demonstrate that pitavastatin was not significantly different than atorvastatin in lowering LDL-C in patients with type 2 diabetes mellitus and mixed dyslipidemia.

Table 9 Lipid Response by Dose of Pitavastatin and Atorvastatin in Patients with Type 2 Diabetes Mellitus and Mixed Dyslipidemia in Study 305 (Mean % Change from Baseline at Week 12)
Treatment | N | LDL-C | Apo-B | TC | TG | HDL-C | non-HDL-C
Pitavastatin 4 mg daily | 274 | -41 | -32 | -28 | -20 | 7 | -36
Atorvastatin 20 mg daily | 136 | -43 | -34 | -32 | -27 | 8 | -40

The treatment differences in efficacy in LDL-C change from baseline between pitavastatin and active controls (i.e., atorvastatin, simvastatin, or pravastatin) in the in the active-controlled studies described above are summarized in Figure 1.

Figure 1 Treatment Difference in Adjusted Mean Percent Change in LDL-C between Pitavastatin and the Comparator (Atorvastatin, Simvastatin, or Pravastatin)

NL=non-inferiority limit.

Pediatric use information is approved for Kowa Co Ltd’s LIVALO (pitavastatin) tablets. However, due to Kowa Co Ltd’s marketing exclusivity rights, this drug product is not labeled with that information.

16 HOW SUPPLIED/STORAGE AND HANDLING

ZYPITAMAG (pitavastatin) Tablets, 2 mg are white to off-white, beveled-edge, round-shaped tablets debossed with “877” on one side and plain on the other side and are supplied as follows:

NDC 25208-201-09 in bottle of 90 tablets with child-resistant closure
NDC 25208-201-15 in bottle of 500 tablets

ZYPITAMAG (pitavastatin) Tablets, 4 mg are white to off-white, beveled-edge, round-shaped tablets
debossed with “878” on one side and plain on the other side and are supplied as follows:

NDC 25208-202-09 in bottle of 90 tablets with child-resistant closure
NDC 25208-202-15 in bottle of 500 tablets

Storage
Store at 20°C to 25°C (68°F to 77°F) [See USP Controlled Room Temperature].
Protect from moisture and light.

17 PATIENT COUNSELING INFORMATION

Myopathy and Rhabdomyolysis

Advise patients that ZYPITAMAG may cause myopathy and rhabdomyolysis. Inform patients that the risk is increased when taking certain types of medication and they should discuss all medication, both prescription and over the counter, with their healthcare provider. Instruct patients to promptly report any unexplained muscle pain, tenderness or weakness particularly if accompanied by malaise or fever [see Warnings and Precautions (5.1)].

Hepatic Dysfunction
Inform patients that ZYPITAMAG may cause liver enzyme elevations and possibly liver failure. Advise patients to promptly report fatigue, anorexia, right upper abdominal discomfort, dark urine or jaundice [see Warnings and Precautions (5.3)].

Increases in HbA1c and Fasting Serum Glucose Levels
Inform patients that increases in HbA1c and fasting serum glucose levels may occur with ZYPITAMAG. Encourage patients to optimize lifestyle measures, including regular exercise, maintaining a healthy body weight, and making healthy food choices [see Warnings and Precautions (5.4)].

Pregnancy
Advise pregnant patients and patients who can become pregnant of the potential risk to a fetus. Advise patients to inform their healthcare provider of a known or suspected pregnancy to discuss if ZYPITAMAG should be discontinued [see Use in Specific Populations (8.1)].

Lactation
Advise patients that breastfeeding is not recommended during treatment with ZYPITAMAG [see Use in Specific Populations (8.2)].

Please address medical inquiries to (medical.information@medicure.com) Tel.: 1-800-509-0544.

This product’s label may have been updated. For current full prescribing information, please visit www.medicure.com

Manufactured by:
Zydus Lifesciences Ltd.

Ahmedabad, India

Distributed by:

Medicure
Princeton, NJ 08540 USA

PIM-ZYP-08

PACKAGE LABEL.PRINCIPAL DISPLAY PANEL

NDC 25208-201-09

Zypitamag (Pitavastatin) Tablets, 2 mg

90 Tablets

Rx only

NDC 25208-201-15

Zypitamag (Pitavastatin) Tablets, 2 mg

500 Tablets in Bottle

Rx only

NDC 25208-202-09

Zypitamag (Pitavastatin) Tablets, 4 mg

90 Tablets

Rx only

NDC 25208-202-15

Zypitamag (Pitavastatin) Tablets, 4 mg

500 Tablets in Bottle

Rx only